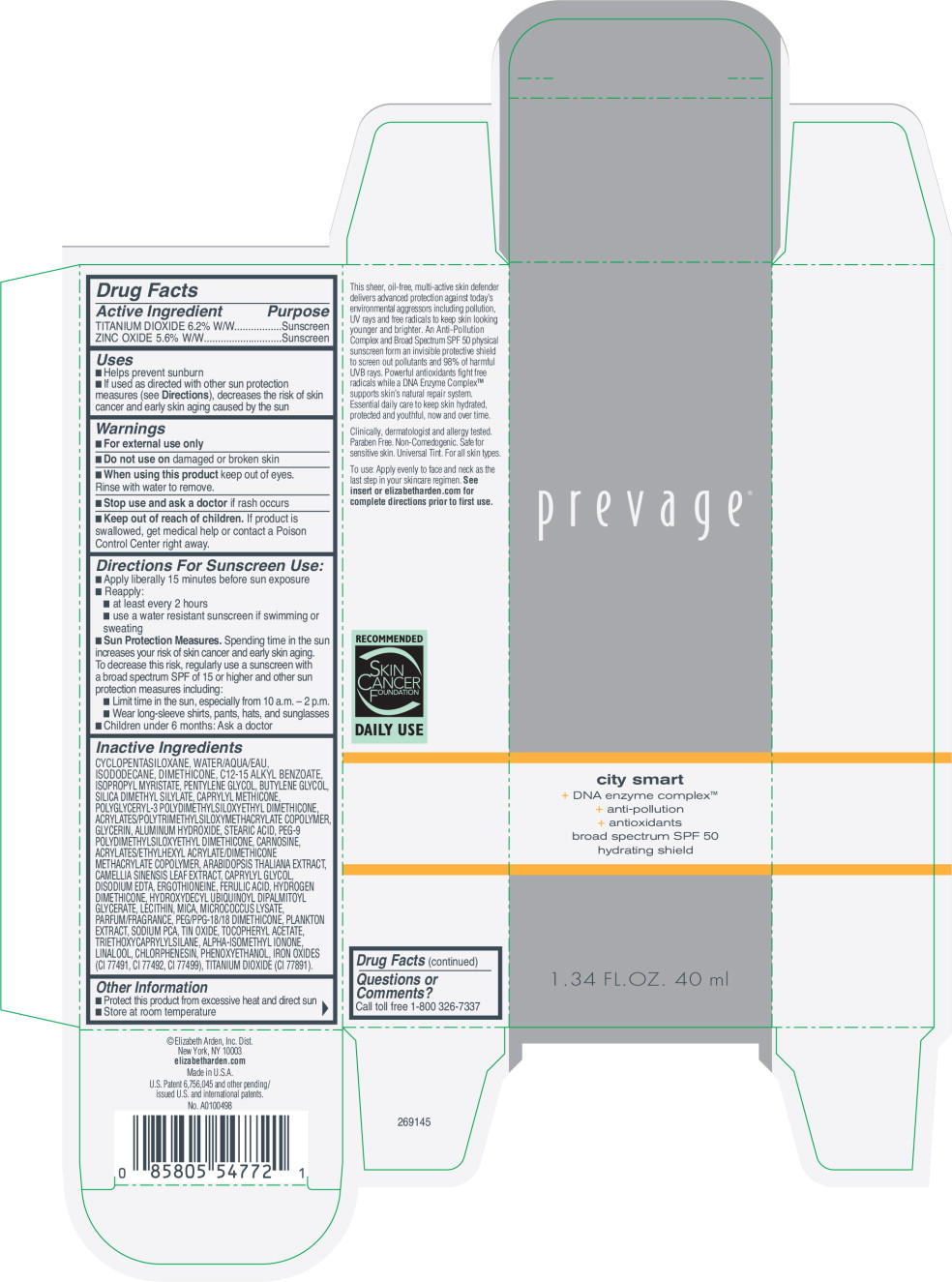 DRUG LABEL: ELIZABETH ARDEN PREVAGE CITY SMART BROAD SPECTRUM SPF 50 HYDRATING SHIELD
NDC: 67938-3050 | Form: LOTION
Manufacturer: ELIZABETH ARDEN, INC
Category: otc | Type: HUMAN OTC DRUG LABEL
Date: 20170801

ACTIVE INGREDIENTS: TITANIUM DIOXIDE .062 g/1 mL; ZINC OXIDE .056 g/1 mL
INACTIVE INGREDIENTS: DIMETHICONE; ALKYL (C12-15) BENZOATE; ISOPROPYL MYRISTATE; PENTYLENE GLYCOL; BUTYLENE GLYCOL; SILICA DIMETHYL SILYLATE; CAPRYLYL TRISILOXANE; GLYCERIN; ALUMINUM HYDROXIDE; STEARIC ACID; PEG-9 POLYDIMETHYLSILOXYETHYL DIMETHICONE; CARNOSINE; PHENOXYETHANOL; MICA; SODIUM PYRROLIDONE CARBOXYLATE; HYDROGEN DIMETHICONE (13 CST); EDETATE DISODIUM; CHLORPHENESIN; .ALPHA.-TOCOPHEROL ACETATE; FERULIC ACID; GREEN TEA LEAF; PEG/PPG-18/18 DIMETHICONE; TRIETHOXYCAPRYLYLSILANE; LECITHIN, SOYBEAN; STANNIC OXIDE; ARABIDOPSIS THALIANA; HYDROXYDECYL UBIQUINOYL DIPALMITOYL GLYCERATE; ERGOTHIONEINE; ISODODECANE; CYCLOMETHICONE 5; WATER

Drug Facts

Active Ingredient

TITANIUM DIOXIDE 6.2% W/W

ZINC OXIDE 5.6% W/W

Purpose

Sunscreen

Sunscreen

Uses

- Helps prevent sunburn
- If used as directed with other sun protection measures (see Directions), decreases the risk of skin cancer and early skin aging caused by the sun

Warnings

- For external use only

- Do not use on damaged or broken skin

- When using this product keep out of eyes. Rinse with water to remove.

- Stop use and ask a doctor if rash occurs

- Keep out of reach of children. If product is swallowed, get medical help or contact a Poison Control Center right away.

Directions For Sunscreen Use:

- Apply liberally 15 minutes before sun exposure
- Reapply:
  - at least every 2 hours
  - use a water resistant sunscreen if swimming or sweating
- Sun Protection Measures. Spending time in the sun increases your risk of skin cancer and early skin aging. To decrease this risk, regularly use a sunscreen with a broad spectrum SPF of 15 or higher and other sun protection measures including:
  - Limit time in the sun, especially from 10 a.m. – 2 p.m.
  - Wear long-sleeve shirts, pants, hats, and sunglasses
- Children under 6 months: Ask a doctor

Inactive Ingredients

CYCLOPENTASILOXANE, WATER/AQUA/EAU, ISODODECANE, DIMETHICONE, C12-15 ALKYL BENZOATE, ISOPROPYL MYRISTATE, PENTYLENE GLYCOL, BUTYLENE GLYCOL, SILICA DIMETHYL SILYLATE, CAPRYLYL METHICONE, POLYGLYCERYL-3 POLYDIMETHYLSILOXYETHYL DIMETHICONE, ACRYLATES/POLYTRIMETHYLSILOXYMETHACRYLATE COPOLYMER, GLYCERIN, ALUMINUM HYDROXIDE, STEARIC ACID, PEG-9 POLYDIMETHYLSILOXYETHYL DIMETHICONE, CARNOSINE, ACRYLATES/ETHYLHEXYL ACRYLATE/DIMETHICONE METHACRYLATE COPOLYMER, ARABIDOPSIS THALIANA EXTRACT, CAMELLIA SINENSIS LEAF EXTRACT, CAPRYLYL GLYCOL, DISODIUM EDTA, ERGOTHIONEINE, FERULIC ACID, HYDROGEN DIMETHICONE, HYDROXYDECYL UBIQUINOYL DIPALMITOYL GLYCERATE, LECITHIN, MICA, MICROCOCCUS LYSATE, PARFUM/FRAGRANCE, PEG/PPG-18/18 DIMETHICONE, PLANKTON EXTRACT, SODIUM PCA, TIN OXIDE, TOCOPHERYL ACETATE, TRIETHOXYCAPRYLYLSILANE, ALPHA-ISOMETHYL IONONE, LINALOOL, CHLORPHENESIN, PHENOXYETHANOL, IRON OXIDES (CI 77491, CI 77492, CI 77499), TITANIUM DIOXIDE (CI 77891).

Other Information

- Protect this product from excessive heat and direct sun
- Store at room temperature

Questions or Comments?

Call toll free 1-800 326-7337

Principal Display Panel - Prevage City Smart Broad Spectrum SPF 50 Hydrating Shield

prevage®

city smart

+ DNA enzyme complex™

+ anti-pollution

+ antioxidants

broad spectrum SPF 50

hydrating shield

1.34 FL. OZ. 40 ml